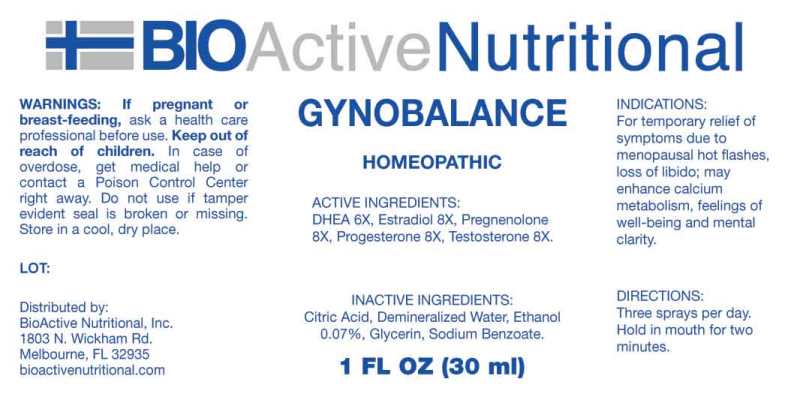 DRUG LABEL: Gynobalance
NDC: 43857-0033 | Form: LIQUID
Manufacturer: BioActive Nutritional, Inc.
Category: homeopathic | Type: HUMAN OTC DRUG LABEL
Date: 20230810
DEA Schedule: CIII

ACTIVE INGREDIENTS: PRASTERONE 6 [hp_X]/1 mL; ESTRADIOL 8 [hp_X]/1 mL; PREGNENOLONE 8 [hp_X]/1 mL; PROGESTERONE 8 [hp_X]/1 mL; TESTOSTERONE 8 [hp_X]/1 mL
INACTIVE INGREDIENTS: ANHYDROUS CITRIC ACID; GLYCERIN; SODIUM BENZOATE; WATER; ALCOHOL

DRUG FACTS:

ACTIVE INGREDIENTS:

DHEA (Dehydroepiandrosterone) 6X, Estradiol 8X, Pregnenolone 8X, Progesterone 8X, Testosterone 8X.

INDICATIONS:

For temporary relief of symptoms due to menopausal hot flashes, loss of libido; may enhance calcium metabolism, feelings of well-being and mental clarity.

WARNINGS:

If pregnant or breast-feeding, ask a health care professional before use.

Keep out of reach of children. In case of overdose, get medical help or contact a Poison Control Center right away.

Do not use if tamper evident seal is broken or missing.

Store in cool, dry place.

Keep out of reach of children. In case of overdose, get medical help or contact a Poison Control Center right away.

DIRECTIONS:

Three sprays per day. Hold in mouth for two minutes.

INDICATIONS:

For temporary relief of symptoms due to menopausal hot flashes, loss of libido; may enhance calcium metabolism, feelings of well-being and mental clarity.

INACTIVE INGREDIENTS:

Citric Acid, Demineralized Water, Ethanol 0.07%, Glycerin, Sodium Benzoate.

QUESTIONS:

Distributed by:
BioActive Nutritional, Inc.
1803 N. Wickham Rd.
Melbourne, FL 32935
bioactivenutritional.com

PACKAGE LABEL DISPLAY:

BIOActive Nutritional

GYNOBALANCE

HOMEOPATHIC

1 FL OZ (30 ml)